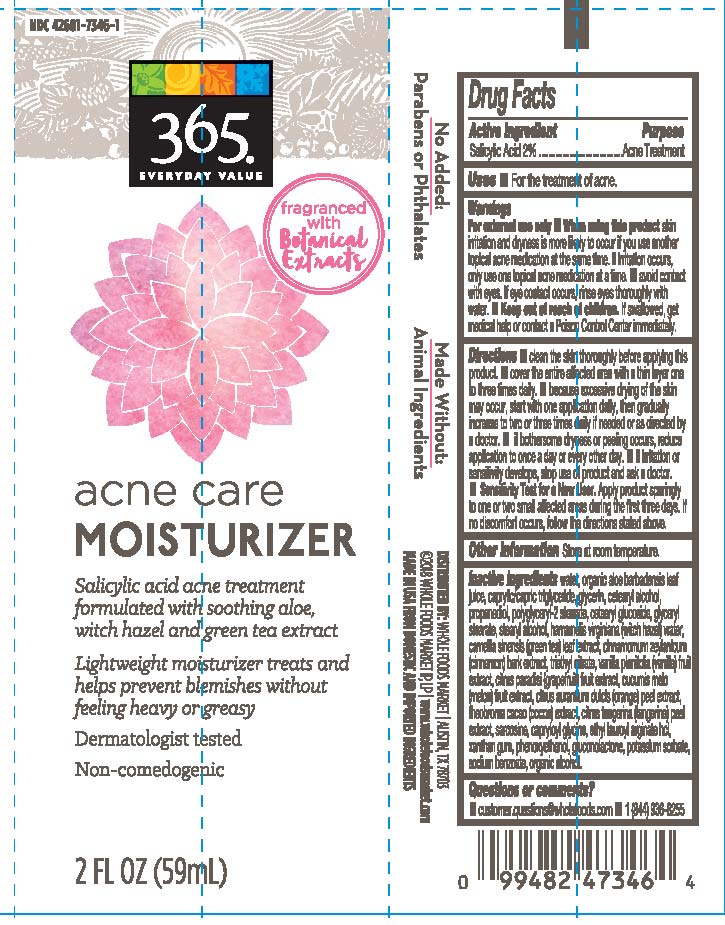 DRUG LABEL: Acne Care Moisturizer
NDC: 42681-7346 | Form: LOTION
Manufacturer: Whole Foods Market
Category: otc | Type: HUMAN OTC DRUG LABEL
Date: 20251230

ACTIVE INGREDIENTS: SALICYLIC ACID 1.18 g/1.18 g
INACTIVE INGREDIENTS: WATER

Acne Care Moisturizer

Active Ingredient

Salicylic Acid 2%

Uses:

For the treatment of acne.

Directions:

Clean the skin thoroughly before applying this product.

Cover the entire affected area with a thin layer one to three times daily.

Because excessive drying of the skin may occur, start with one application daily, then gradually increase to two or three times daily if needed or directed by a doctor.

If bothersome dryness or peeling occurs, reduce application to once a day or every other day.

If irritation or sensitivity develops, stop use of product and ask a doctor.

Sensitivity test for a New User. Apply product sparingly to one or two small affected areas during the first three days. If no discomfort occurs, follow the directions stated above.

Warnings

For external use only

When using this product skin irritation and dryness is likely to occur if you use another topical acne medication at the same time. If irritation occurs, only use one topical acne medication at a time.

Avoid Contact with eyes. If eye contact occurs, rinse eyes thoroughly with water.

Keep out of reach of children. If swallowed, get medical help or contact a Poison Control Center immediately.

Keep out of reach of children. If swallowed, get medical help or contact a Poison Control Center immediately.

Purpose

Acne Treatment

Inactive Ingredients

water, organic aloe barbadensis leaf juice, caprylic/capric triglyceride, glycerin, cetearyl alcohol, propanediol, polyglyceryl-2 stearate, cetearyl glucoside, glyceryl stearate, stearyl alcohol, hamamelis virginiana (witch hazel) water, camellia sinensis (green tea) leaf extract, cinnamomum zeylanicum (cinnamon) bark extract, triethyl citrate, vanilla planifolia (vanilla) fruit extract, citrus paradisi (grapefruit) fruit extract, cucumis melo (melon) fruit extract, citrus aurantium dulcis (orange) peel extract, theobroma cacao (cocoa) extract, citrus tangerina (tangerine) peel extract, sarcosine, capryloyl glycine, ethyl lauroyl arginate hcl, xanthan gum, phenoxyethanol, gluconolactone, potassium sorbate, sodium benzoate, organic alcohol.

Questions or comments?

customer.questions@wholefoods.com

1 (844) 936-8255